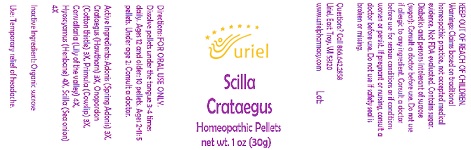 DRUG LABEL: Scilla Crataegus
NDC: 48951-8382 | Form: PELLET
Manufacturer: Uriel Pharmacy Inc.
Category: homeopathic | Type: HUMAN OTC DRUG LABEL
Date: 20210802

ACTIVE INGREDIENTS: HAWTHORN LEAF WITH FLOWER 3 [hp_X]/1 1; HYOSCYAMUS NIGER LEAF 4 [hp_X]/1 1; ONOPORDUM ACANTHIUM FLOWER 3 [hp_X]/1 1; DRIMIA MARITIMA BULB 4 [hp_X]/1 1; ADONIS VERNALIS FLOWERING TOP 3 [hp_X]/1 1; PRIMULA VERIS FLOWER 3 [hp_X]/1 1; CONVALLARIA MAJALIS 4 [hp_X]/1 1
INACTIVE INGREDIENTS: SUCROSE

Scilla Crataegus

INDICATIONS AND USAGE

Directions: FOR ORAL USE ONLY.

DOSAGE AND ADMINISTRATION

Dissolve pellets under the tongue 3-4 times daily. Ages 12 and older: 10 pellets. Ages 2-11: 5 pellets. Under age 2: Consult a doctor.

ACTIVE INGREDIENT

Active Ingredients: Adonis (Spring Adonis) 3X, Crataegus (Hawthorn) 3X, Onopordon (Cotton thistle) 3X, Primula (Cowslip) 3X,
Convallaria (Lily of the valley) 4X, Hyoscyamus (Henbane) 4X, Scilla (Sea onion) 4X

Inactive Ingredient: Organic sucrose

PURPOSE

Use: Temporary relief of headache.

KEEP OUT OF REACH OF CHILDREN.

WARNINGS

Warnings: Claims based on traditional homeopathic practice, not accepted medical evidence. Not FDA evaluated. Contains sugar. Diabetics and persons intolerant of sucrose (sugar): Consult a doctor before use. Do not use if allergic to any ingredient.Consult a doctor before use for serious conditions or if conditions worsen or persist. If pregnant or nursing, consult a doctor before use.
Do not use if safety seal is broken or missing.

Questions? Call 866.642.2858
Uriel, East Troy, WI 53120
www.urielpharmacy.com Lot: